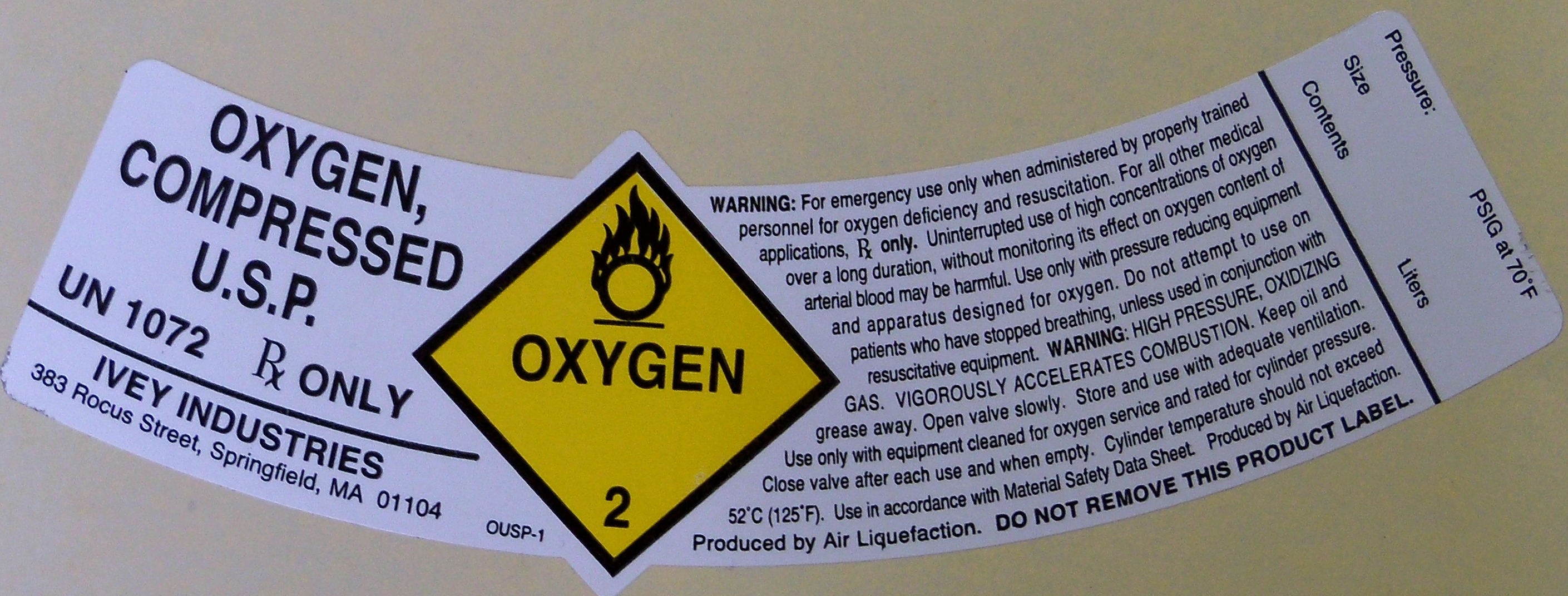 DRUG LABEL: OXYGEN
NDC: 55065-001 | Form: GAS
Manufacturer: Ivey Industries
Category: prescription | Type: HUMAN PRESCRIPTION DRUG LABEL
Date: 20100423

ACTIVE INGREDIENTS: OXYGEN 992 L/1000 L

OXYGEN COMPRESSED USP LABEL

PACKAGE LABEL

OXYGEN COMPRESSED USP
UN 1072 RX ONLY
IVEY INDUSTRIES 383 ROCUS STREET SPRINGFILED MA 01104